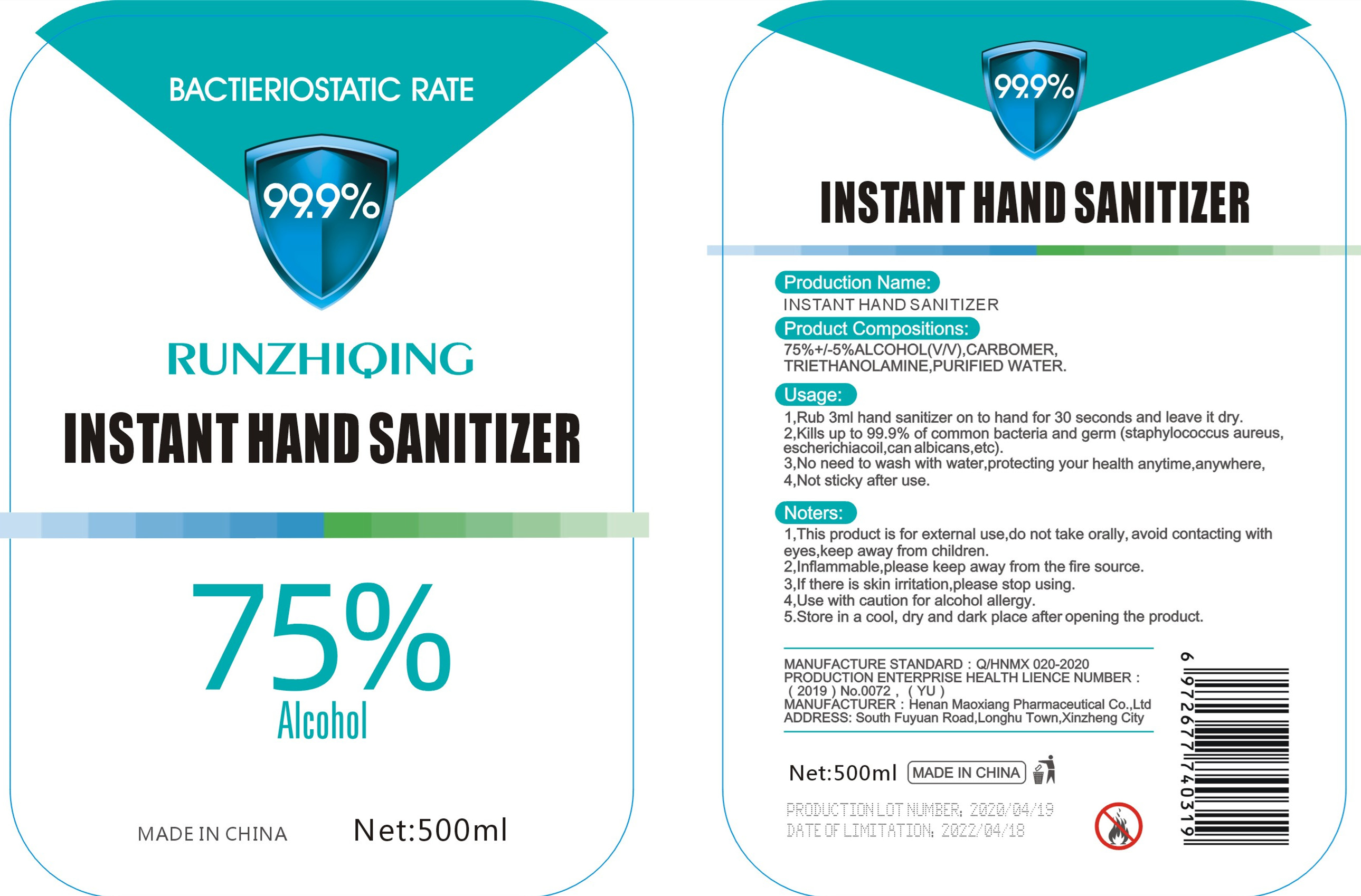 DRUG LABEL: INSTANT HAND SANITIZER
NDC: 41071-001 | Form: LIQUID
Manufacturer: Henan Maoxiang Pharmaceutical Co., Ltd.
Category: otc | Type: HUMAN OTC DRUG LABEL
Date: 20200427

ACTIVE INGREDIENTS: ALCOHOL 375 mL/500 mL
INACTIVE INGREDIENTS: WATER; TROLAMINE; CARBOMER COPOLYMER TYPE A (ALLYL PENTAERYTHRITOL CROSSLINKED)

INACTIVE INGREDIENT

Purified water

Medical carbomer

Medical triethanolamine

ACTIVE INGREDIENT

Alcohol

keep out of reach of children

PURPOSE

Disinfection
Sterilization
No Rinseing

DOSAGE AND ADMINISTRATION

Store inacool, dryand dark place after openingthe product.

INDICATIONS AND USAGE

Rub 3ml hand santier onto hand for 30 seconds and leave it dry.

WARNINGS

1.This product is for external use, do not take orally avoid contactingwitheyes, keep away from children.
2.Inflammable, please keep away fromthe fre source.
3.if there is skin itatin, please stop using.
4.Use withcaution for alcohol alery
5.Store inacool, dryand dark place after openingthe product.